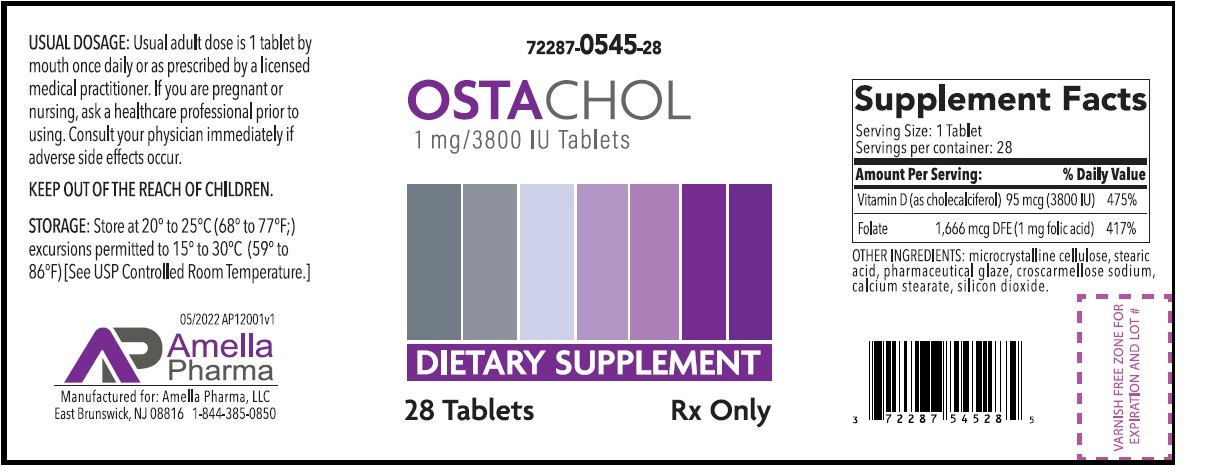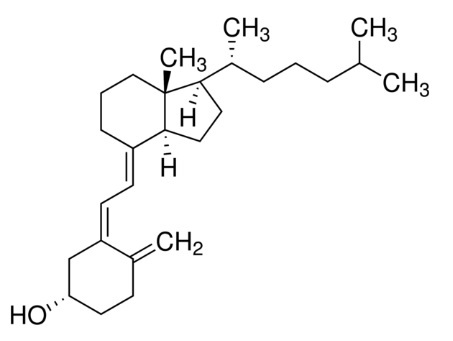 DRUG LABEL: OSTACHOL
NDC: 72287-545 | Form: TABLET
Manufacturer: Amella Pharma LLC
Category: other | Type: Dietary Supplement
Date: 20220616

ACTIVE INGREDIENTS: CHOLECALCIFEROL 0.095 mg/1 1; FOLIC ACID 1 mg/1 1
INACTIVE INGREDIENTS: MICROCRYSTALLINE CELLULOSE; STEARIC ACID; SHELLAC; CROSCARMELLOSE SODIUM; CALCIUM STEARATE; SILICON DIOXIDE

OSTACHOL

Rx Only OSTACHOL Tablets Dietary Supplement Dispensed by Prescription**

Supplement Facts
Serving Size:1 Tablet
Servings per container: 28
Amount Per Serving: | % Daily Value
Vitamin D (as cholecalciferol) 95 mcg (3800 IU) | 475%
Folate 1,666 mcg DFE (1 mg folic acid) | 417%

OTHER INGREDIENTS: microcrystalline cellulose, stearic acid, pharmaceutical glaze, croscarmellose sodium, calcium stearate, silicon dioxide.

STATEMENT OF IDENTITY
OSTACHOL Tablets is an orally administered prescription folate product for the dietary management of patients with unique nutritional needs requiring increased folate levels and Vitamin D supplementation due to Vitamin D deficiency and other nutritional supplementation. OSTACHOL should be administered under the supervision of a licensed medical practitioner.

OSTACHOL tablets are supplied as a light yellow tablet with “A1” imprinted on one side.

Vitamin D3 (cholecalciferol) is a white, crystalline powder, very soluble in water, with the following structural formula:

Each tablet contains:

Folic Acid............................................... 1,666 mcg DFE (1 mg)
Vitamin D3 (Cholecalciferol).......................... 95 mcg (3800IU)

Each tablet contains the following inactive ingredients: microcrystalline cellulose, stearic acid, pharmaceutical glaze, croscarmellose sodium, calcium stearate, and silicon dioxide.

The in vivo synthesis of the major biologically active metabolites of vitamin D occurs in two steps. The first hydroxylation of ergocalciferol takes place in the liver (to 25-hydroxyvitamin D) and the second in the kidneys (to 1,25-dihydroxyvitamin D). Vitamin D metabolites promote the active absorption of calcium and phosphorus by the small intestine, thus elevating serum calcium and phosphate levels sufficiently to permit bone mineralization. Vitamin D metabolites also mobilize calcium and phosphate from bone and probably increase the reabsorption of calcium and perhaps also of phosphate by the renal tubules.

There is a time lag of 10 to 24 hours between the administration of vitamin D and the initiation of its action in the body due to the necessity of synthesis of the active metabolites in the liver and kidneys. Parathyroid hormone is responsible for the regulation of this metabolism in the kidneys.

HEALTH CLAIM:

OSTACHOL is used for dietary management of patients with unique nutritional needs requiring increased folate levels, Vitamin D deficiency or are in need of Vitamin D supplementation and other nutritional supplementation.

OSTACHOL can be taken by women of childbearing age, pregnant women, and lactating and nonlactating mothers.

PRECAUTIONS

CONTRAINDICATIONS:

This product is contraindicated in patients with known hypersensitivity to any of the ingredients.

PRECAUTIONS:

KEEP OUT OF THE REACH OF CHILDREN.

Tell your doctor if you have: kidney problems, thyroid disease. This medication should be used as directed during pregnancy or while breast-feeding. Consult your doctor about the risks and benefits.

Folic acid alone is improper therapy in the treatment of pernicious anemia and other megaloblastic anemias where vitamin B12 is deficient. Folic acid in doses above 0.1 mg daily may obscure pernicious anemia in that hematologic remission can occur while neurological manifestations progress.

ADVERSE REACTIONS

Allergic sensitization has been reported following both oral and parenteral administration of folic acid. You should call your doctor for medical advice about serious adverse events. You may report adverse side effects to Amella Pharma, LLC, at 1-844-385-0850.

DOSAGE AND ADMINISTRATION:

Take one tablet daily or as directed by a healthcare practitioner.

If you are pregnant or nursing, ask a healthcare professional prior to using. Consult your physician immediately if adverse side effects occur.

KEEP OUT OF THE REACH OF CHILDREN.

HOW SUPPLIED:

OSTACHOL tablets are supplied as a light yellow tablet with “A1” imprinted on one side.

OSTACHOL Tablets is dispensed in child-resistant bottles as the following:
72287-545-28* 28ct bottle

Store at 20°-25°C (68°-77°F); excursions permitted to 15°-30°C (59°-86°F) [See USP Controlled Room Temperature.]

Protect from heat, light and moisture.

Tamper Evident: Do not use if seal is broken or missing.

Manufactured for:
Amella Pharma, LLC
E Brunswick, NJ 08816 1-844-385-0850

Issued: 05/2022 AP12001v1

*Amella Pharma does not represent these product codes to be National Drug Codes (NDC). Product codes are formatted according to standard industry practice, to meet the formatting requirement by pedigree reporting and supply-chain control including pharmacies.

** This product is a prescription-folate with or without other dietary ingredients that – due to increased folate levels (AUG 2 1973 FR 20750), requires an Rx on the label because of increased risk associated with masking of B12 deficiency (pernicious anemia). Based on our assessment of the risk of obscuring pernicious anemia, this product requires licensed medical supervision, an Rx status, and a National Drug Code (NDC) – or similarly-formatted product code, as required by pedigree reporting requirements and supply-chain control as well as – in some cases, for insurance-reimbursement applications.
All prescriptions using this product shall be pursuant to state statutes as applicable. This is not an Orange Book product. This product may be administered only under a physician’s supervision. There are no implied or explicit claims on therapeutic equivalence.